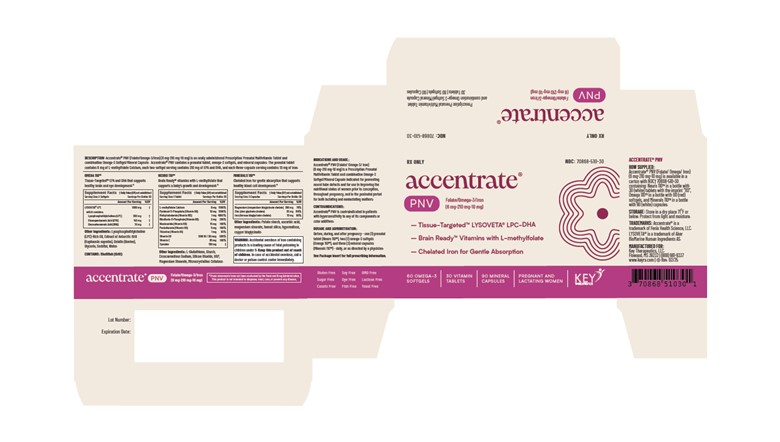 DRUG LABEL: Accentrate PNV
NDC: 70868-510 | Form: KIT | Route: ORAL
Manufacturer: Key Therapeutics
Category: prescription | Type: HUMAN PRESCRIPTION DRUG LABEL
Date: 20250310

ACTIVE INGREDIENTS: TYROSINE 150 ug/1 1; PANTOTHENIC ACID 15 mg/1 1; METHYLCOBALAMIN 1 mg/1 1; CHOLECALCIFEROL 1200 [USP'U]/1 1; THIAMINE 1 mg/1 1; LEVOMEFOLATE CALCIUM 6 mg/1 1; RIBOFLAVIN 5'-PHOSPHATE 3 mg/1 1; PYRIDOXAL 5-PHOSPHATE 10 mg/1 1; NIACINAMIDE 5 mg/1 1; ASCORBIC ACID 85 ug/1 1; 1-STEAROYL-SN-GLYCERO-3-PHOSPHOCHOLINE 260 ug/1 1; EICOSAPENTAENOIC ACID 140 ug/1 1; DOCOSAHEXAENOIC ACID 70 ug/1 1; FERROUS BISGLYCINATE 10 mg/1 1; MAGNESIUM GLYCINATE 290 mg/1 1; ZINC GLYCINATE 35 mg/1 1
INACTIVE INGREDIENTS: MAGNESIUM STEARATE; SILICON DIOXIDE; CROSCARMELLOSE SODIUM; GLUTATHIONE; CELLULOSE, MICROCRYSTALLINE; STARCH, POTATO; GELATIN TYPE B BOVINE (160 BLOOM); WATER; GLYCERIN; SORBITOL; EUPHAUSIA KRILL; ASCORBIC ACID; COPPER GLYCINATE; SILICA; STARCH, POTATO; HYPROMELLOSES

DESCRIPTION

Accentrate® PNV (Folate/Omega-3/Iron) (6 mg-210 mg-10 mg) is an orally administered Prescription Prenatal Multivitamin Tablet and combination Omega-3 Softgel/Mineral Capsule. Accentrate® PNV contains a prenatal tablet, omega-3 softgels, and mineral capsules. Each one tablet contains 6 mg of L-methylfolate Calcium, each two softgel serving contains 210 mg of EPA and DHA, and each three capsule serving contain 10 mg of iron.

Each prenatal tablet contains:

L-methylfolate Calcium | 6 mg
Pyridoxal-5-phosphate (Vitamin B6) | 10 mg
Methylcobalamin (Vitamin B12) | 1 mg
Riboflavin-5-phosphate (Vitamin B2) | 3 mg
Niacinamide (Vitamin B3) | 5 mg
Pantothenate (Vitamin B5) | 15 mg
Thiamine (Vitamin B1) | 1 mg
Vitamin D3 | 1200 IU / 30 mcg
Vitamin C | 85 mg
Tyrosine | 150 mg
Other Ingredients: L-Glutathione, Starch, Croscarmellose Sodium, Silicon Dioxide, USP, Magnesium Stearate, Microcrystalline Cellulose.

Each two omega-3 softgel serving contains:

LYSOVETA® LPC; which contains | 1000 mg
Lysophosphatidylcholine (LPC) | 260 mg
Eicosapentaenoic Acid | 140 mg
Docosahexaenoic Acid | 70 mg
Other Ingredients: Lysophosphatidylcholine (LPC)-Rich Oil, Extract of Antarctic Krill (Euphausia superba), Gelatin (bovine), Glycerin, Sorbitol, Water.

CONTAINS: Shellfish (Krill)

Each three mineral capsule serving contains:

Magnesium (magnesium glycinate chelate) | 290 mg
Zinc (zinc glycinate chelate) | 35 mg
Iron (ferrous bisglycinate chelate) | 10 mg
Other Ingredients: Potato starch, ascorbic acid, magnesium stearate, fumed silica, hypomellose, copper bisglycinate.

INDICATIONS AND USAGE

Accentrate® PNV (Folate/Omega-3/Iron) (6 mg-210 mg-10 mg) is a Prescription Prenatal Multivitamin Tablet and combination Omega-3 Softgel/Mineral Capsule indicated for preventing neural tube defects and use in improving the nutritional status of women prior to conception, throughout pregnancy, and in the postnatal period for both lactating and nonlactating mothers.

PREGNANCY AND NURSING MOTHERS

Accentrate® PNV is intended for women of childbearing age who are – or desire to become, pregnant regardless of lactation status. Accentrate® PNV may be preferred for women at risk of dysregulated dopamine or serotonin regulation, which may include depression as a result of folate or cobalamin deficiency as well as folate-induced postpartum depression, or are at risk of folate-induced birth defects such as may be found with spina bifida and other neural tube defects (NTDs). It has been shown that folate enhances the synthesis and/or regeneration of tetrahydrobiopterin (BH4), which is an essential cofactor in the biosynthesis of monoamine neurotransmitters serotonin, dopamine and norepinephrinei, ii, iii. The conversion of tryptophan to serotonin also requires BH4.

Accentrate® PNV may also be an appropriate source of folate for those at high risk of NTDs because of the amount and bioavailability of L-methylfolate contained therein. Accentrate® PNV is Pregnancy Category A; however, Accentrate® PNV is NOT a standard complete prenatal/postnatal supplement for the following reasons:

Accentrate® PNV contains over 1,000% of DV of folate for pregnant and lactating women, which may or may not be important depending upon your genetic disposition and previous pregnancies; please consult with your licensed medical practitioner on advanced folate supplementation during pregnancy for women at risk of NTDs and/or suboptimal folate/depression/postpartum.

Accentrate® PNV contains over 600% of DV for cobalamin for pregnant and lactating women.

Accentrate® PNV contains less than have the DV–only 37%–of iron for pregnant and lactating women, and Accentrate® PNV does not contain other vitamins and minerals that might be more suitable to your specific metabolic needs or part of a standard prenatal/postnatal multivitamin/multimineral/dietary supplement.iv, v, vi, vii

DOSAGE AND ADMINISTRATION

The usual adult dose may be taken as one (1) white vitamin tablet (Neuro 110™), two (2) red omega-3 softgels (Omega 110™), and three (3) white mineral capsules (Minerals 110™) daily, before, during and after pregnancy, or as directed by a physician.

FOLATE is essential for the production of certain coenzymes in many metabolic systems such as purine and pyrimidine synthesis. About 70% of food folate and cellular folate is comprised of L-methylfolate. It is the primary form of folate in circulation, and is also the form transported across membranes – particularly across the blood brain barrier – into peripheral tissues. In the cell, L-methylfolate is used in the remethylation of homocysteine to form methionine and tetrahydrofolate (THF). L-methylfolate is converted into functional, metabolically active coenzyme forms for use in the body, and supplies the active folate substrate, THF (tetrahydrofolate) for use in transformylation and methylation biochemistry.

Folates are best known for reducing the incidence of fetal neural tube defects (NTDs).viii, ix,x NTDs are congenital malformations produced by failure of the neural tube to form and close properly during embryonic development.xi,xii During the first four weeks of pregnancy – when many women do not even realize that they have conceived, adequate maternal folate intake is essential to reduce the risk of NTDs. Folate is also essential in the synthesis and maintenance of nucleoprotein in erythropoiesis. It also promotes white blood cell (WBC) and platelet production in folate-deficiency anemia. Folate is associated with methylation and transformylation biochemistry. Folate is involved in transformylation and methylation metabolism as well as, indirectly, succinylation metabolism (through the “methyl trap” hypothesis). Folate plays a central role in the formation of nucleic acid precursors, such as thymidylic acid and purine nucleotides, which are essential for nucleic acid synthesis and cell division. IOM/NAS (1998) noted that the evidence for a protective effect from folate supplements is much stronger than that for food folate. Other ingredients are added to folate as cofactors, coenzymes and co-metabolites; in studies by Czeizel and Dudas (1992) and Berry et al. (1999), factors other than folate intake may affect the magnitude of risk reduction or participate in a co-protective effect with folate.^4,5

L-methylfolate supplementation increases the formation of endothelian nitric oxide synthase resulting in increase nitric oxide. This causes vasodilation to the nerves, increasing blood supply to the nerves, and reducing vascular oxidative stress.xiv L-methylfolate supplementation also increases nitric oxide levels by increasing the amount of tetrahydrobioterin (BH4). BH4 is required for nitric oxide synthesis.xv

FOLATE COENZYMES, COFACTORS, AND COMETABOLITES - The following ingredients are added to enhance the bioavailable potential of folate, and include:

COBALAMIN - Methylcobalamin is required for two important reactions: the conversion of methylmalonyl CoA to succinyl CoA, a Krebs cycle intermediate, and the conversion of homocysteine to methionine, a reaction in which the methyl group of L-methylfolate is donated to remethylate homocysteine. Homocysteine has been found to stimulate or alter transcription factors involved in inflammation, with an important ancillary consequence of BH4 depletion. For example, it has been reported that homocysteine-mediated activation of sterol regulatory element binding protein (SREBP) upregulates expression of 3-hydroxy-3-methyl-glutaryl-coenzyme (HMG-CoA reductase) with increased biosynthesis and cellular uptake of cholesterol, the depletion of BH4 being a secondary effect.

PYRIDOXAL-5’-PHOSPHATE (PLP) is the active form of vitamin B. The amino acid decarboxylase considered to decarboxylate both dihydroxyphenylalanine (DOPA) and 5-hydroxytryptophan (5-HTP) requires pyridoxal phosphate as coenzyme. Deficient levels of plasma PLP are significantly associated with depressive symptomatology in human studies.xvi

OTHER B VITAMINS - Thiamine pyrophosphate (TPP) is the biologically active derivative of thiamine, vitamin B Flavin adenine dinucleotide (FAD) is the active substrate of riboflavin, vitamin B . It has been reported that deficiencies of thiamine and riboflavin are associated with depressive symptoms. , Nicotinamide adenine dinucleotide (NADH) is a reduced form of niacin, or vitamin B Niacin-dependent dihydropteridine reductase (DHPR) is involved in BH regeneration.

IRON – Accentrate® PNV supplies iron as a pure amino acid iron-chelate, which provides pure elemental iron – an essential component in the formation of hemoglobin. Iron therapy is necessary in advanced folate supplementation due to interference between iron and folate metabolism. Sufficient amounts are required for effective erythropoiesis. According to the USDA, “The impact of iron deficiency on folate metabolism is most dramatic during the reproductive and neonatal stages of the life cycle.”

Iron is one of the primary cofactors in BH reactions. Tyrosine hydroxylase requires iron and tetrahydrobiopterin to catalyze the conversion of tyrosine (also contained in Accentrate® PNV) to DOPA, which is then converted to dopamine by the enzyme DOPA decarboxylase. Dopamine β-hydroxylase transforms dopamine to norepinephrine, which can be further transformed to epinephrine.

OMEGA-3 FATTY ACIDS - Docosahexaenoic acid (DHA) and eicosapentaenoic acid (EPA) are omega-3 fatty acids. Accentrate® PNV contains LYSOVETA® LPC which comprises the omega-3 fatty acid-derivatives EPA and DHA conjugated to lysophosphatidylcholine (LPC). LPC-EPA and LPC-DHA are the forms of EPA and DHA that is absorbed by the brain through the MSFD2a receptor active on the blood brain barrier. Accretion of EPA and DHA in LPC form has been shown to be significantly higher than triglyceride, phospholipid (PC), and free fatty acid form.

DHA bound to LPC was shown to be 4 times higher in umbilical circulation than maternal circulation, which may indicate that omega-3 fatty acids in LPC form is preferred for omega-3 supplementation during pregnancy. Evidence suggests that LYSOVETA® LPC provides a neuroprotective effect against neonatal brain injury.xxii

FOLATE REGULATION: The Federal Register Notices from 1971 to 1973 establish that increased folate is proper supplement in megaloblastic anemias of tropical and nontropical sprue, nutritional origin, pregnancy, infancy, and childhood.xxiii,xxiv,xxv Folate metabolism may be affected by malabsorption issues that differ widely among population groups. The March 5, 1996 Federal Register Notice (61 FR 8760) states “The agency concluded that the scientific literature did not support the superiority of any one source of folate over others, and that the data were insufficient to provide a basis for stating that a specific amount of folate is more effective than another amount [emphasis added].xxvi The actual amount and source of folate require the supervision of a licensed medical practitioner to achieve a satisfactory maintenance level, and may exceed the 0.8 mg UL. The Federal Register Notice of August 2, 1973 (38 FR 20750) specifically states that “dietary supplement preparations are available without a prescription (21 CFR 121.1134). Levels higher than dietary supplement amounts are available only with a prescription. Oral preparations supplying more than 0.8 mg of folate per dosage unit would be restricted to prescription dispensing and that a dietary supplement furnishing 0.8 mg could be prescribed when a maintenance level of 0.8 mg per day was indicated. When clinical symptoms have subsided and the blood picture and/or CSF folate levels have become normal, a maintenance level should be used. “Patients should be kept under supervision of a licensed practitioner and adjustment of the maintenance level made if relapse appears imminent. In the presence of alcoholism, hemolytic anemia, anticonvulsant therapy, or chronic infection, the maintenance level may need to be increased [emphasis added]. ” In the Letter Regarding Dietary Supplement Health Claim for Folic Acid, Vitamin B6, and Vitamin B12 and Vascular Disease (Docket No. 99P-3029) dated November 28, 2000, FDA wrote “... high intakes of folate may partially and temporarily correct pernicious anemia while the neurological damage of vitamin B12 deficiency progresses. IOM/NAS (1998) set the UL for all adults of 1 mg per day because of devastating and irreversible neurological consequences of vitamin B12 deficiency, the data suggesting that pernicious anemia may develop at a younger age in some racial or ethnic groups, and the uncertainty about the extent of the occurrence of vitamin B12 deficiency in younger age groups (IOM/NAS, 1998) [emphasis added].xxviii”

Summary: This product is a Prescription Prenatal Multivitamin Tablet containing folate that, due to advanced folate levels, requires administration under the care of a licensed medical practitioner. "Rx Only" on the label is to ensure prescription dispensing and that the product is administered under the supervision of a licensed medical practitioner due to the increased risk associated with masking of B12 deficiency (pernicious anemia). The “Rx Only” status and a National Drug Code (NDC), or similar Product Code, facilitate pedigree reporting requirements and supply-chain control as well as, in some cases, insurance-reimbursement applications.

CONTRAINDICATIONS

This product is contraindicated in patients with a known hypersensitivity to any of the articles contained in this product. This product is contraindicated for individuals with conditions for which any of the ingredients are contraindicated.

Iron therapy is contraindicated in patients with hemochromatosis and patients with iron storage disease or the potential for iron storage disease due to chronic hemolytic anemia (e.g., inherited anomalies of hemoglobin structure or synthesis and/or red cell enzyme deficiencies, etc.), pyridoxine responsive anemia, or cirrhosis of the liver.

WARNING

Accidental overdose of iron-containing products is a leading cause of fatal poisoning in children under 6. Keep this product out of reach of children. In case of accidental overdose, call a doctor or a Poison Control Center immediately .

WARNINGS/PRECAUTIONS:

Caution is recommended in patients with a family history of bipolar illness. Mood elevation is possible in this population.

Caution is also recommended in patients taking anticonvulsant medications as folate may interfere with anticonvulsant medication, and may lower seizure threshold. Furthermore, it has been reported that anticonvulsant medications interfere with folate metabolism, but the exact action is unclear; therefore caution is recommended with patients in this therapeutic group.

Patients undergoing cancer treatment should consult their licensed medical practitioner for advice.

Folate alone is improper therapy in the treatment of pernicious anemia and other megaloblastic anemias where vitamin B12 is deficient. Folate in doses above 0.1 mg daily may obscure pernicious anemia in that hematologic remission may occur while neurological manifestations progress. Daily ingestion of more than 3 grams per day of omega-3 fatty acids (DHA, ALA, and EPA) may have potential antithrombotic activities, or effects, and may increase bleeding times. Administration of omega-3 fatty acids, including DHA, should be avoided in patients with inherited or acquired bleeding diathesis, including those taking anticoagulants. Exercise caution to ensure that the prescribed dosage of DHA does not exceed 1 gram (1000 mg) per day.

ADVERSE REACTIONS

Allergic reactions have been reported following the use of oral and parenteral folate.xxix Mild transient diarrhea, polycythemia vera, itching, transitory exanthema, and the feeling of swelling of the entire body have been associated with methylcobalamin.xxx Allergic reactions, acne, skin reactions, photosensitivity, nausea, vomiting, abdominal pain, loss of appetite, paresthesia, somnolence, nausea, and headaches have been associated with pyridoxal-5’-phosphate.xxxi

Call your medical practitioner about side effects. You may report side effects to the FDA at 1-800- FDA-1088 or call Key Therapeutics, LLC. at 888-981-8337.

DRUG INTERACTIONS

Talk to your licensed medical practitioner, healthcare practitioner, personal physician, and/or pharmacist before taking or using any prescription, over-the-counter medicines, or herbal/health supplements alongside this product. Drugs which may interact with folate include:

• Antiepileptic drugs (AED): The AED class including, but not limited to, phenytoin, carbamazepine, primidone, valproic acid, fosphenytoin, valproate, phenobarbital and lamotrigine have been shown to impair folate absorption and increase the metabolism of circulating folate.

• Additionally, concurrent use of folic acid has been associated with enhanced phenytoin metabolism, lowering the level of the AED in the blood and allowing breakthrough seizures to occur. Caution should be used when prescribing this product among patients who are receiving treatment with phenytoin and other anticonvulsants.

• Cholestyramine: Reduces folic acid absorption and reduces serum folate levels.

• Colestipol: Reduces folic acid absorption and reduces serum folate levels. Cycloserine: Reduces folic acid absorption and reduces serum folate levels.

• Fluoxetine: Fluoxetine exerts a noncompetitive inhibition of the 5-methyltetrahydrofolate active transport in the intestine.

• Isotretinoin: Reduced folate levels have occurred in some patients taking isotretinoin.

• L-dopa, triamterene, colchicine, and trimethoprim may decrease plasma folate levels.

• Nonsteroidal Anti-inflammatory Drugs (NSAIDs): NSAIDs have been shown to inhibit some folate dependent enzymes in laboratory experiments.

• NSAIDs include ibuprofen, naproxen, indomethacin and sulindac.

• Oral Contraceptives: Serum folate levels may be depressed by oral contraceptive therapy.

• Methylprednisolone: Reduced serum folate levels have been noted after treatment with methylprednisolone.

• Pancreatic Enzymes: Reduced serum folate levels have occurred in some patients taking pancreatic extracts, such as pancreatin and pancrelipase.

• Pentamidine: Reduced folate levels have been seen with prolonged intravenous pentamidine.

• Pyrimethamine: High levels of folic acid may result in decreased serum levels of pyrimethamine.

• Smoking and Alcohol: Reduced serum folate levels have been noted.

• Sulfasalazine: Inhibits the absorption and metabolism of folic acid. Metformin treatment in patients with type 2 diabetes decreases serum folate.

• Warfarin can produce significant impairment in folate status after a 6-month therapy.

Caution should be exercised with the concomitant use of folinic acid and trimethoprim- sulfamethoxazole for the acute treatment of Pneumocystis carinii pneumonia in patients with HIV infection as it is associated with increased rates of treatment failure and mortality in a placebo-controlled study.

Drugs which may interact with vitamin B12 (Methylcobalamin):

• Antibiotics, cholestyramine, colchicines, colestipol, metformin, para-aminosalicylic, and potassium chloride may decrease the absorption of vitamin B12.

• Nitrous oxide can produce a functional vitamin B12 deficiency

*These statements have not been evaluated by the Food and Drug Administration. This product is not intended to diagnose, treat, cure, or prevent any disease.

HOW SUPPLIED

Accentrate® PNV (Folate/Omega/Iron) (6 mg-210 mg-10 mg) is available in a carton with NDC† 70868-510-30 containing: Neuro 110™ in a bottle with 30 (white) tablets with the imprint “110”, Omega 110™ in a bottle with 60 (red) softgels, and Minerals 110™ in a bottle with 90 (white) capsules.

†This product is a prescription folate with or without other dietary ingredients, due to increased folate levels (AUG 2 1973 FR 20750). The “Rx” on the label is to ensure prescription dispensing and that the product is administered under the supervision of a licensed medical practitioner due to the increased risk associated with masking of B12 deficiency (pernicious anemia).

Based on the risk of obscuring pernicious anemia, this product requires supervision of a licensed medical practitioner. The “Rx Only” status and a National Drug Code (NDC), or similar Product Code, facilitate pedigree reporting requirements and supply-chain control as well as, in some cases, insurance-reimbursement applications.

FOR THE PHARMACIST

This product is not an Orange Book (OB) rated product, therefore all prescriptions using this product shall be pursuant to state statutes as applicable. There are no claims of bioequivalence or therapeutic equivalence.

This product may, under certain circumstances, be dispensed through a certified mail-order program as long as there is record of prescription AND confirmation that the patient is under the supervision of a licensed medical practitioner.

STORAGE AND HANDLING

Store in a dry place at 71°F or below. [See USP]. Protect from light and moisture. Dispense in a tight, light-resistant container. KEEP THIS PRODUCT OUT OF THE REACH OF CHILDREN.

MANUFACTURED for Key Therapeutics, LLC. Flowood, MS 39232

NDC: 70868-510-30 Accentrate® PNV combo kit is packaged in a carton containing each bottle separately:

NDC: 70868-511-30 Prenatal Multivitamin Tablets as Accentrate® Neuro 110,

Product Code: 70868-512-60 Omega-3 softgels as Accentrate® Omega 110, and

Product Code: 70868-513-90 Mineral capsules as Accentrate® Minerals 110.

MADE IN USA

Trademarks: Accentrate® is a trademark of Fenix Health Science, LLC. LYSOVETA® LPC is a trademark of Aker BioMarine Human Ingredients AS.

Distributed by Key Therapeutics, LLC. in partnership with Fenix Health Science, LLC.

Key Therapeutics, LLC. Fenix Health Science, LLC.

232 Market Street 1000 Parkwood Cir. SE

Building K Number 252 Suite 900

Flowood, MS 39232 Atlanta, GA 30339

www.keyrx.com www.fenixhealthscience.com

© Rev. 02/25

Accentrate® PNV (Folate/Omega/Iron) (6 mg-210 mg-10 mg)

Prescription Prenatal Multivitamin Tablet and combination Omega-3 Softgel/Mineral Capsule

NDC: 70868-510-30

Rx Only

REFERENCES

i Miller AL. “The methylation, neurotransmitter, and antioxidant connections between folate and depression.” Altern Med Rev. 2008 Sep;13(3):216-26.

ii Bottiglieri T, et al. “Homocysteine, folate, methylation, and monoamine metabolism in depression.” J Neurol Neurosurg Psychiatry. 2000 Aug; 69(2):228-32.

iii Young SN. “Folate and depression a – neglected problem.” J Psychiatry Neurosci 2007 March; 32(2):80-82.

iv Letter Regarding Dietary Supplement Health Claim for Folic Acid, Vitamin B6, and Vitamin B12 and Vascular Disease (Docket No. 99P3029). November 28, 2000.

v Letter Regarding Dietary Supplement Health Claim for Folic Acid With Respect to Neural Tube Defects (Docket No. 91N-100H). October 10, 2000.

vi Hendler SS, Rorvik D, eds. PDR for Nutritional Supplements. Montvale, NJ: Thomson Healthcare; 2001.

vii Hendler SS, Rorvik D. PDR for Nutritional Supplements. 2nd ed. Montvale, NJ. Physicians’ Desk Reference Inc; 2008.

viii Hendler SS, Rorvik D, eds. PDR for Nutritional Supplements. Montvale, NJ: Thomson Healthcare; 2001. 10.

ix Hendler SS, Rorvik D. PDR for Nutritional Supplements. 2nd ed. Montvale, NJ. Physicians’ Desk Reference Inc; 2008. 11.

x Bendich A, “Preventive Nutrition: The Comprehensive Guide for Health Professionals.” 2009. Dietary Supplement Facts Regulations at http://www.fda.gov/Food/GuidanceRegulation/GuidanceDocumentsRegulatoryInformation/DietarySupplements/ucm2006823.htm.

xi Letter Regarding Dietary Supplement Health Claim for Folic Acid With Respect to Neural Tube Defects. October 10, 2000.

xii Veves A. et al. Diabetes 1998. 47:457-463

xiii Verhaar, MC. Atherosclerosis, Thrombosis, Vascular Biology, 2001.

xv Federal Register Notice of April 9, 1971 (36 FR 6843).

xvi Federal Register Notice of August 2, 1973 (38 FR 20750).

xvii Letter Regarding Dietary Supplement Health Claim for Folic Acid, Vitamin B6, and Vitamin B12 and Vascular Disease. November 28, 2000.

xvii Zhang G, et al. “Thiamine nutritional status and depressive symptoms are inversely associated among older Chinese adults.” J Nutr. 2013 Jan;143(1):53-8.

xviii Naghashpour M, et al. “Riboflavin status and its association with serum hs-CRP levels among clinical nurses with depression.” J Am Coll Nutr. 2011 Oct;30(5):340-7.

xix Nguyen, L., et al. “Mfsd2a is a transporter for the essential omega-3 fatty acid DHA in the brain.” Nature, 509 (2014). (7501), 503–506.

xx Sugasini, D. “Enrichment of brain docosahexaenoic acid (DHA) is highly dependent upon the molecular carrier of dietary DHA: lysophosphatidylcholine is more efficient than either phosphatidylcholine or triacylglycerol.” J Nutr Biochem. 2019 Dec; 74:108231.

xxi Ferchaud-Roucher, V, et al. "A potential role for lysophosphatidylcholine in the delivery of long chain polyunsaturated fatty acids to the fetal circulation." Biochimica et Biophysica Acta (BBA)-Molecular and Cell Biology of Lipids 1864.3 (2019): 394-402.

xxii Hermans, E, et al. “Dietary LPC-Bound n-3 LCPUFA Protects against Neonatal Brain Injury in Mice but Does Not Enhance Stem Cell Therapy.” Nutrients 16.14 (2024): 2252.

xxiii Federal Register Notice of April 9, 1971 (36 FR 6843).

xxiv Federal Register Notice of August 2, 1973 (38 FR 20750).

xxv Federal Register Notice of October 17, 1980 (45 FR 69043 at 69044).

xxvi Federal Register Notice of March 5, 1996 (61 FR 8760).

xxvii Federal Register Notice of August 2, 1973 (38 FR 20750).

xxviii Letter Regarding Dietary Supplement Health Claim for Folic Acid, Vitamin B6, and Vitamin B12 and

Vascular Disease (Docket No. 99P3029). November 28, 2000.

xxix Natural Standard Research Collaboration (NIH). Folate (folic acid) Monograph 2009.

xxx Natural Standard Research Collaboration (NIH). Vitamin B12 Monograph 2009.

xxxi Alternative Medicine Review Vitamin B6 Monograph Volume 6, Number 1, 2001.